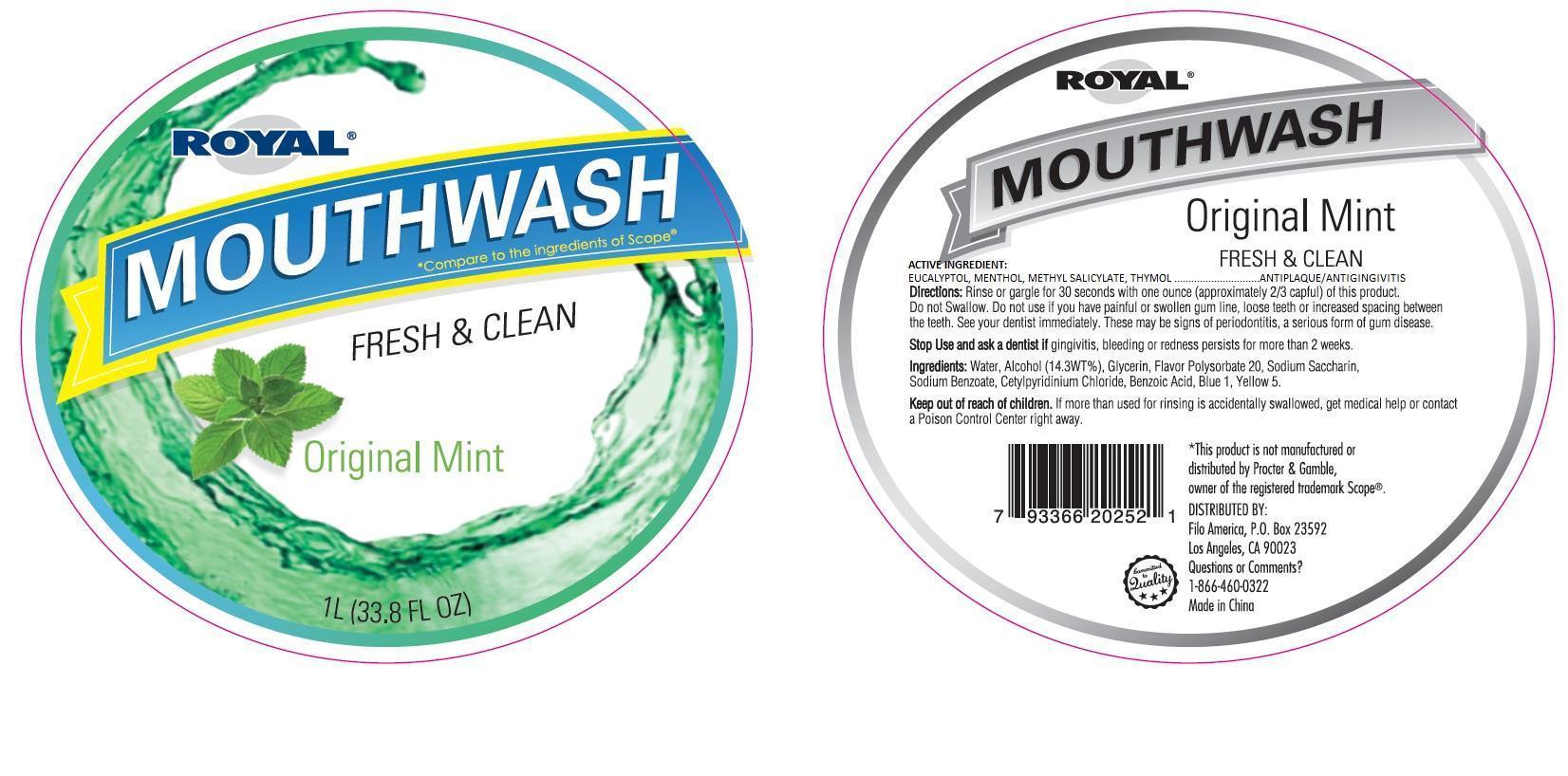 DRUG LABEL: Royal Mouthwash Fresh and Clean Original Mint
NDC: 50438-304 | Form: LIQUID
Manufacturer: Filo America
Category: otc | Type: HUMAN OTC DRUG LABEL
Date: 20130917

ACTIVE INGREDIENTS: EUCALYPTOL 0.92 mg/1 mL; MENTHOL 0.42 mg/1 mL; METHYL SALICYLATE 0.6 mg/1 mL; THYMOL 0.64 mg/1 mL
INACTIVE INGREDIENTS: WATER; ALCOHOL; SORBITOL; POLOXAMER 407; BENZOIC ACID; SACCHARIN SODIUM; SODIUM BENZOATE; FD&C YELLOW NO. 5; FD&C BLUE NO. 1

DRUG FACTS

ACTIVE INGREDIENT

EUCALYPTOL 0.092%, MENTHOL 0.042%, METHYL SALICYLATE 0.060%, THYMOL 0.064%

PURPOSE

ANTIPLAQUE/ANTIGINGIVITIS

USES

TO HELP CONTROL PLAQUE THAT LEADS TO GINGIVITIS.

WARNINGS

DO NOT USE IF YOU HAVE PAINFUL OR SWOLLEN GUM LINE, LOOSE TEETH OR INCREASED SPACING BETWEEN THE TEETH. SEE YOUR DENTIST IMMEDIATELY. THESE MAY BE SIGNS OF PERIODONTITIS, A SERIOUS FORM OF GUM DISEASE.

DO NOT USE FOR CHILDREN UNDER 12 YEARS OF AGE.

STOP USE AND ASK A DENTIST IF GINGIVITIS, BLEEDING OR REDNESS PERSISTS FOR MORE THAN 72 HOURS.

KEEP OUT OF REACH OF CHILDREN

IF MORE THAN USED FOR RINSING IS ACCIDENTALLY SWALLOWED, GET MEDICAL HELP OR CONTACT A POISON CONTROL CENTER RIGHT AWAY.

DIRECTIONS

ADULTS AND CHILDREN 12 YEARS OF AGE AND OLDER.

VIGOROUSLY SWISH 20 ML (2/3 FLUID OUNCE OR 4 TEASPOONFULS) BETWEEN TEETH FOR 30 SECONDS THEN SPI9T OUT;DO NOT SWALLOW.

CHILDREN UNDER 12 YEARS OF AGE, CONSULT A DENTIST OR DOCTOR.

THIS RINSE IS NOT INTENDED TO REPLACE BRUSHING OR FLOSSING.

OTHER INFORMATION

COLD WATER MAY CLOUD THIS PRODUCT. ITS ANTISEPTIC PROPERTIES ARE NOT AFFECTED. STORE AT ROOM TEMPERATURE (59°-77°F).

INACTIVE INGREDIENTS:

WATER (AQUA), ALCOHOL (21.6%), SORBITOL SOLUTION, FLAVOR, POLOXAMER 407, BENZOIC ACID, SODIUM SACCHARIN, SODIUM BENZOATE, YELLOW 5, BLUE 1